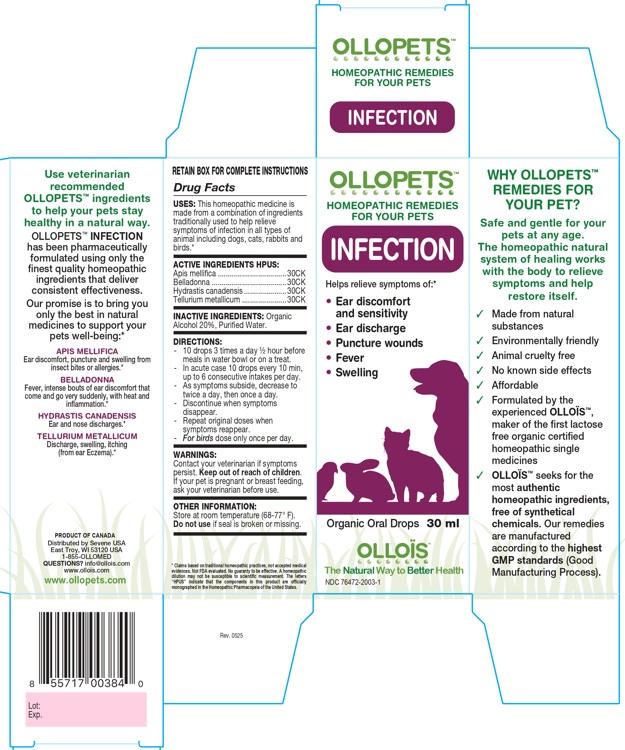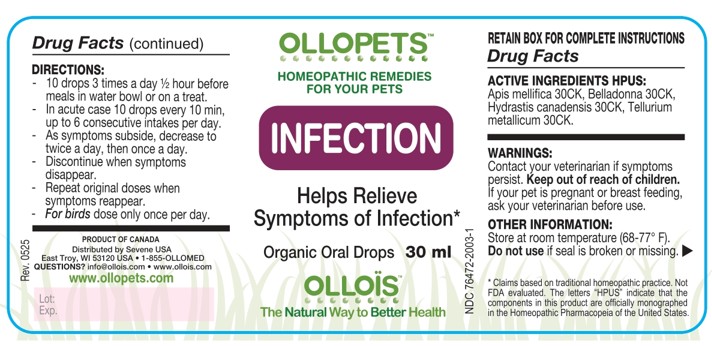 DRUG LABEL: OLLOPETS INFECTION
NDC: 76472-2003 | Form: SOLUTION
Manufacturer: SEVENE USA
Category: homeopathic | Type: OTC ANIMAL DRUG LABEL
Date: 20260218

ACTIVE INGREDIENTS: APIS MELLIFERA 30 [hp_C]/100 mL; ATROPA BELLADONNA 30 [hp_C]/100 mL; GOLDENSEAL 30 [hp_C]/100 mL; TELLURIUM 30 [hp_C]/100 mL
INACTIVE INGREDIENTS: ALCOHOL; WATER

SEVENE USA - OLLOPETS - INFECTION

ACTIVE INGREDIENT HPUS

Apis mellifica ..................................30CK
Belladonna .....................................30CK
Hydrastis canadensis .....................30CK
Tellurium metallicum ......................30CK